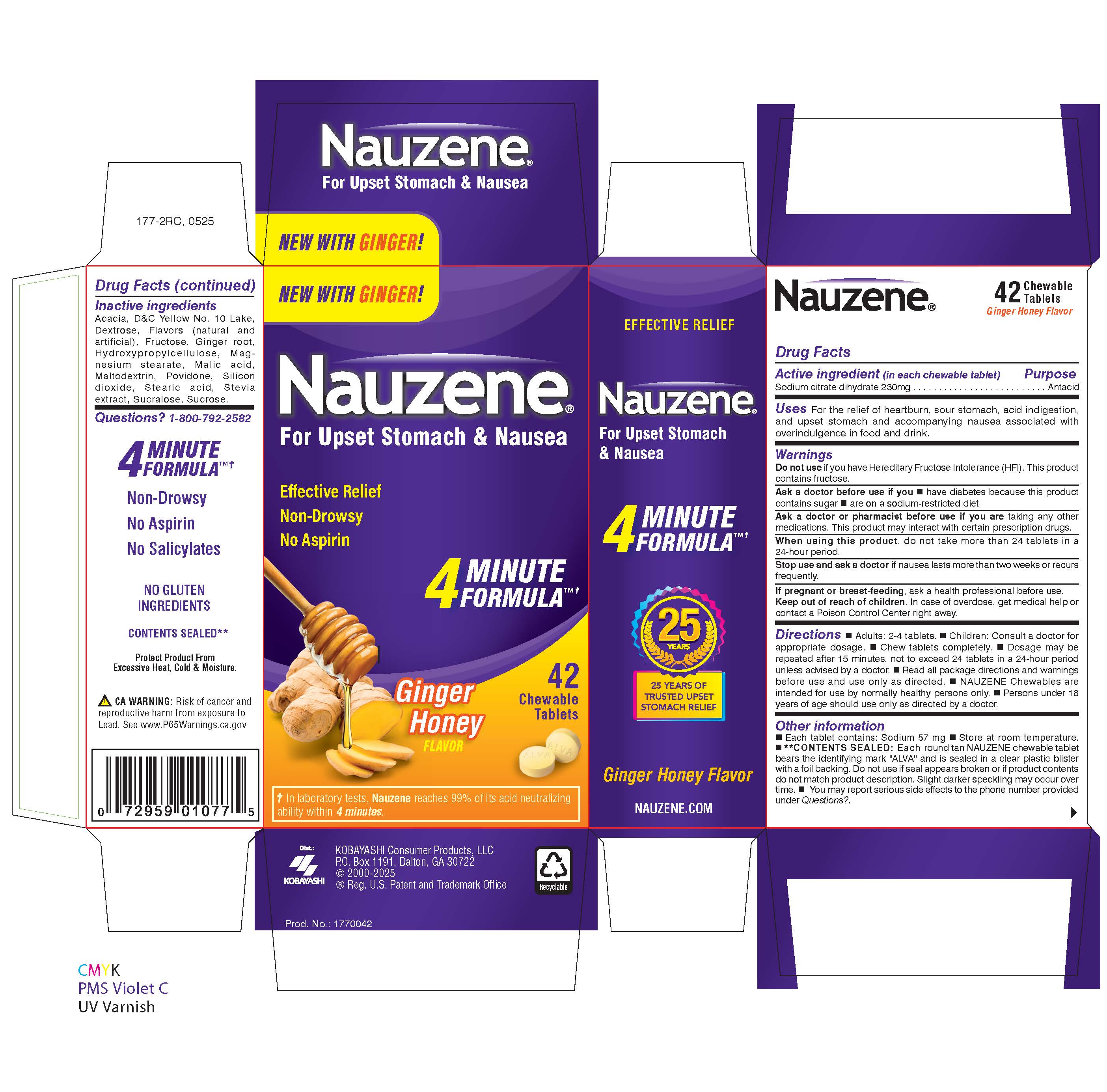 DRUG LABEL: Nauzene Chewables
NDC: 52389-677 | Form: TABLET, CHEWABLE
Manufacturer: Kobayashi Healthcare International, Inc.
Category: otc | Type: HUMAN OTC DRUG LABEL
Date: 20250624

ACTIVE INGREDIENTS: TRISODIUM CITRATE DIHYDRATE 230 mg/1 1
INACTIVE INGREDIENTS: DEXTROSE; POVIDONE K30; MALIC ACID; STEVIA LEAF; ACACIA; HYDROXYPROPYLCELLULOSE; SUCROSE; MAGNESIUM STEARATE; SUCRALOSE; D&C YELLOW NO. 10 ALUMINUM LAKE; FRUCTOSE; STEARIC ACID; ZINGIBER OFFICINALE WHOLE; SILICON DIOXIDE; MALTODEXTRIN

Nauzene Chewables Ginger Honey

Active ingredient (in each cheable tablet)

Sodium citrate dihydrate 230 mg

Purpose

Antacid

Uses

For the relief of heartburn, sour stomach, acid indigestion, and upset stomach and accompanying nausea associated with overindulgence in food and drink.

Do not use

if you have Hereditary Fructose Intolerance (HFI). This product cnotains fructose.

Ask a doctor before use if you

- have diabetes because this product contains sugar
- are on a sodium-restricted diet

Ask a doctor or pharmacist before use if you are

taking any other medications. This product may interact with certain prescription drugs.

When using this product,

do not take more than 16 tablets in a 24-hour period.

Stop use and ask a doctor if

nausea lasts more than two weeks or recurs frequently.

If pregnant or breast-feeding,

ask a health professional before use.

Keep out of reach of children.

In case of overdose, get medical help or contact a Poison Control Center right away.

Directions

- Adults: 2-4 tablets.
- Children: Consult a doctor for appropriate dosage.
- Chew tablets completely.
- Dosage may be repeated after 15 minutes, not to exceed 16 tablets in a 24-hour period unless advised by a doctor.
- Read all package directions and warnings before use and use only as directed.
- Nauzene Chewables are intended for use by normally healthy persons only.
- Persons under 18 years of age should use only as directed by a doctor.

Other information

- Sodium content: 60 mg/tablet
- Store at room temperature.
- **Contents Sealed: Each round tan NAUZENE chewable tablet bears the identifying mark "ALVA" and is sealed in a clear plastic blister with a foil backing. Do not use if seal appears broken or if product contents do not match product description. Slight darker speckling may occur over time. Note: NAUZENE is not intended as a substitute for a balanced nutritional diet or as an electrolyte replensihment.
- You may report serious side effects to the phone number provided under Questions? below.

Inactive ingredients

Acacia, D&C Yellow No. 10 Lake, Dextrose, Flavors (natural and artificial), Fructose, Ginger root, Hydroxypropylcellulose, Magnesium stearate, Malic acid, Maltodextrin, Povidone, Silicon dioxide, Stearic acid, Stevia extract, Sucralose, Sucrose.

Questions?

1-800-792-2582